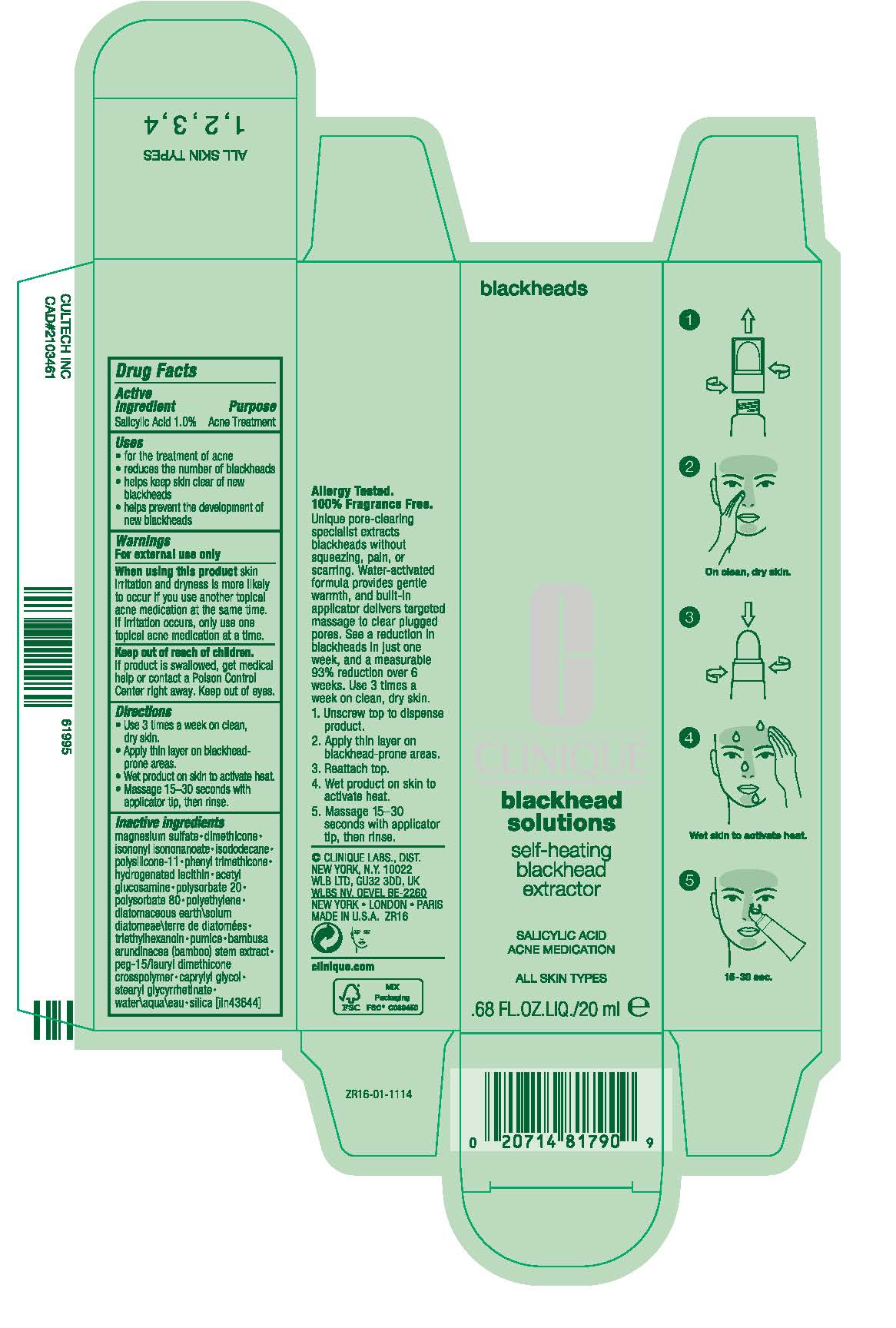 DRUG LABEL: blackhead solutions self-heating blackhead extractor acne medication
NDC: 49527-061 | Form: CREAM
Manufacturer: CLINIQUE LABORATORIES LLC
Category: otc | Type: HUMAN OTC DRUG LABEL
Date: 20241225

ACTIVE INGREDIENTS: SALICYLIC ACID 10 mg/1 mL
INACTIVE INGREDIENTS: DIMETHICONE/VINYL DIMETHICONE CROSSPOLYMER (SOFT PARTICLE); BAMBUSA BAMBOS STEM; MAGNESIUM SULFATE, UNSPECIFIED FORM; DIMETHICONE; ISONONYL ISONONANOATE; ISODODECANE; PHENYL TRIMETHICONE; HYDROGENATED SOYBEAN LECITHIN; N-ACETYLGLUCOSAMINE; POLYSORBATE 20; POLYSORBATE 80; HIGH DENSITY POLYETHYLENE; DIATOMACEOUS EARTH; TRIETHYLHEXANOIN; PUMICE; CAPRYLYL GLYCOL; STEARYL GLYCYRRHETINATE; WATER; SILICON DIOXIDE

blackhead solutions self-heating blackhead extractor acne medication

Drug Facts

Active ingredient

Salicylic Acid 1.0%

Purpose

Acne Treatment

Uses

- reduces the number of blackheads
- helps keep skin clear of new blackheads
- helps prevent development of new blackheads

Warnings

For external use only

When using this product skin irritation and dryness is more likely to occur if you use another topical acne medication at the same time. If irritation occurs, only one topical acne medication should be used unless directed by a doctor.

Keep out of reach of children. If product is swallowed, get medical help or contact a Poison Control Center right away. Keep out of eyes.

Directions

- Use 3 times a week on clean, dry skin.
- Unscrew top to dispense product.
- Apply thin layer on blackhead-prone areas.
- Reattach top.
- Wet product on skin to activate heat.
- Massage 15-30 seconds with applicator tip, then rinse.

Inactive ingredients

magnesium sulfate • dimethicone • isononyl isononanoate • isododecane • polysilicone-11 • phenyl trimethicone • hydrogenated lecithin • acetyl glucosamine • polysorbate 20 • polysorbate 80 • polyethylene • diatomaceous earth\solum diatomeae\terre de diatomées • triethylhexanoin • pumice • bambusa arundinacea (bamboo) stem extract • peg-15/lauryl dimethicone crosspolymer • caprylyl glycol • stearyl glycyrrhetinate • water\aqua\eau • silica [iln43644]

PRINCIPAL DISPLAY PANEL - 20 ml Tube Carton

blackheads

CLINIQUE

blackhead
solutions

self-heating
blackhead
extractor

SALICYLIC ACID
ACNE MEDICATION

ALL SKIN TYPES

.68 FL.OZ.LIQ./20 ml e